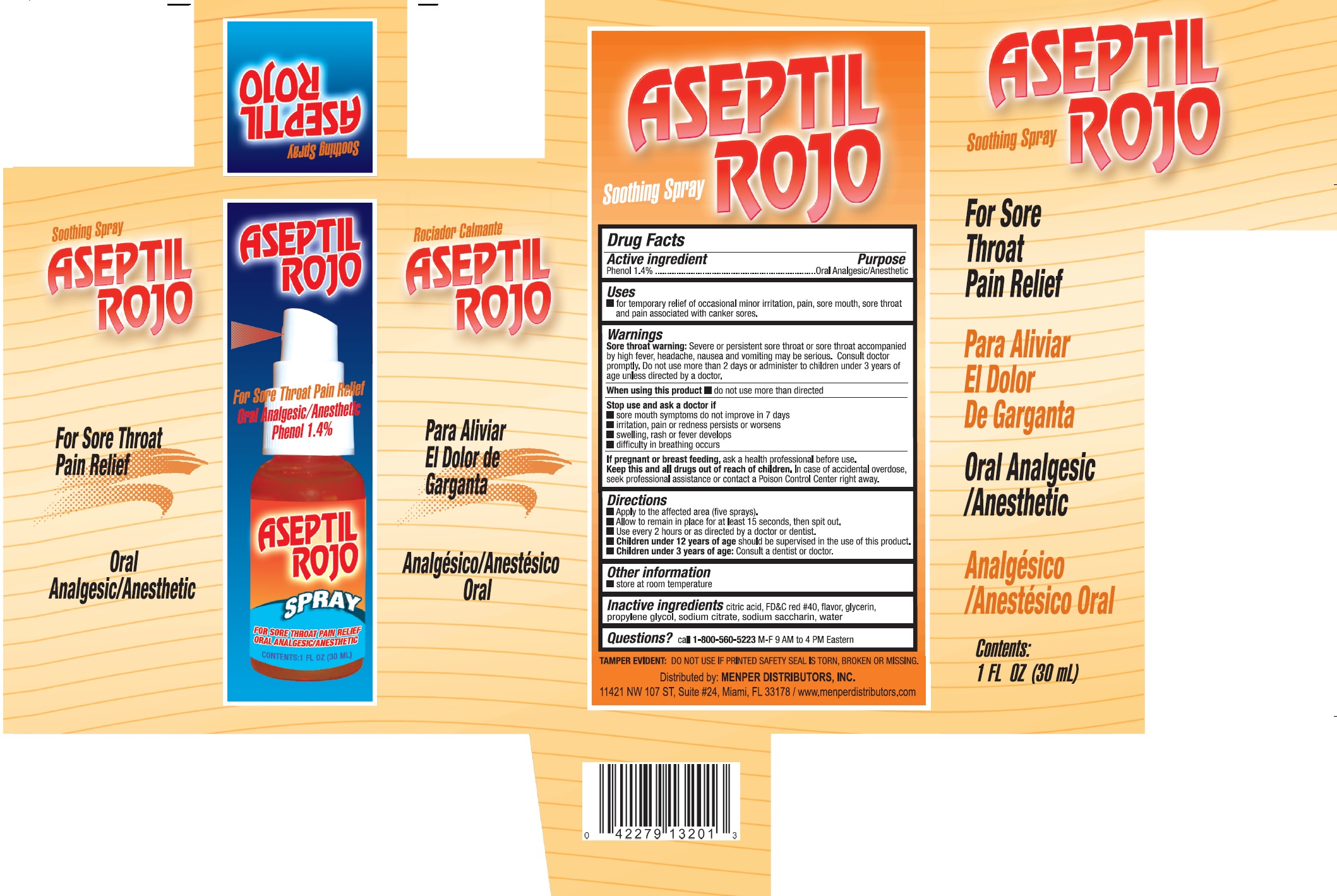 DRUG LABEL: Aseptil Rojo
NDC: 53145-004 | Form: SPRAY
Manufacturer: Menper Distributors, Inc.
Category: otc | Type: HUMAN OTC DRUG LABEL
Date: 20250722

ACTIVE INGREDIENTS: PHENOL 1.4 mg/100 mL
INACTIVE INGREDIENTS: CITRIC ACID ACETATE; FD&C RED NO. 40; GLYCERIN; SACCHARIN SODIUM; PROPYLENE GLYCOL; SODIUM CITRATE; WATER

Aseptil Rojo

Active Ingredient

Phenol 1.4%

Purpose

Oral Analgesic/Anesthetic

Uses

- for temporary relief of occasional minor irritation, pain, sore mouth, sore throat and pain associated with canker sores.

Warnings

Sore throat warning: Sever or persistent sore throat or sore throat accompanied by high fever, headache, nausea and vomiting may be serious. Consult doctor promptly. Do not use more than 2 days or administer to children under 3 years of age unless directed by a doctor.

When using this product do not use more thani directed

Stop use and ask a doctor if

- sore mouth symptoms do not improve in 7 days
- irritation, pain or redness persists or worsens
- swelling, rash or fever develops
- difficulty in breathing occurse

PREGNANCY OR BREAST FEEDING

If pregnant or breast feeding, ask a health professional befre use.

KEEP OUT OF REACH OF CHILDREN

Keep this and all drugs out of reach of children. In case of accidental overdose, seek professional assistance or contact a Poison Control Center right away.

Directions

- Apply to the affected area (five sprays)
- Allow to remain in place for at least 15 seconds, then spit out.
- Use every 2 hours or as directed by a doctor or dentist.
- Children under 12 years of ageshould be supervised in the use of the product.
- Children under 3 years of age:Consult a dentist or doctor.

Inactive ingredients

- citric acid, FD&C red #40, flavor, glycerin, propylene glycol, sodium citrate, saccharin sodium, water.

QUESTIONS

Questions? call 1-800-560-5223 M-F 9 AM to 4 PM Eastern